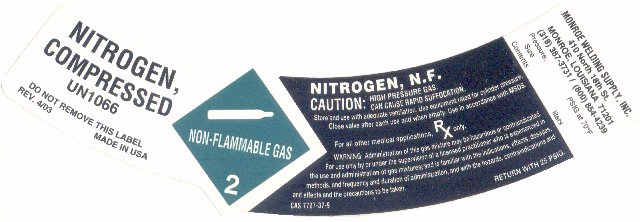 DRUG LABEL: nitrogen
NDC: 52233-003 | Form: GAS
Manufacturer: Monroe Welding Supply, Inc.
Category: prescription | Type: HUMAN PRESCRIPTION DRUG LABEL
Date: 20100824

ACTIVE INGREDIENTS: nitrogen 992 mL/1 L

PACKAGE LABEL

NITROGEN, COMPRESSED NF
UN 1066
DO NOT REMOVE THIS LABEL REV. 4/03 MADE IN USA
NITROGEN, NF
CAUTION: HIGH PRESSURE GAS. CAN CAUSE RAPID SUFFOCATION. Store and use with adequate ventilation. Use equipment rated for cylinder pressure. Close valve after each use and when empty. Use in accordance with MSDS.
For all other medical applications, Rx Only.
WARNING: Administration of this gas mixture may be hazardous and contraindicated. For use only by or under the supervision of a licensed practitioner who is experienced in the use and administration of gas mixtures, and is familiar with the indications, effects, dosages, methods, and frequency and duration of administration, and with the hazards, contraindications and effects and the precautions to be taken.
CAS:7727-37-9
RETURN WITH 25 PSIG
17033 (R 04/05)
MONROE WELDING SUPPLY, INC.
410 N 18TH STREET MONROE, LA 71201
318-387-3731 / 1-800-854-4239
Pressure: PSIG AT 70F
Size
Contents liters